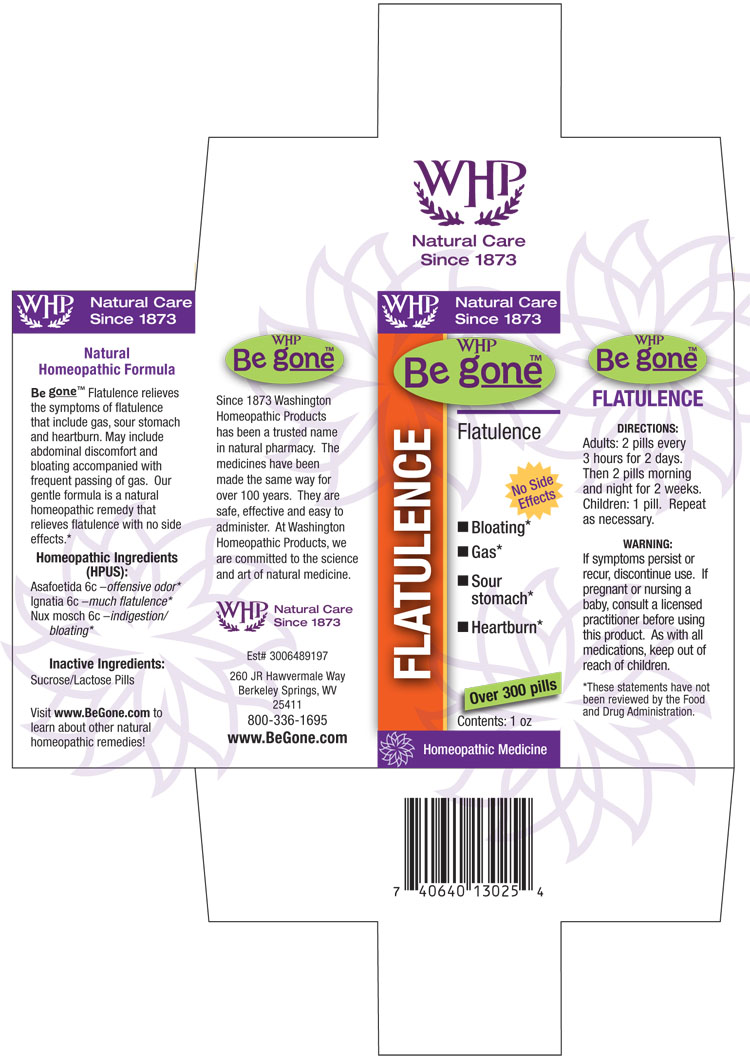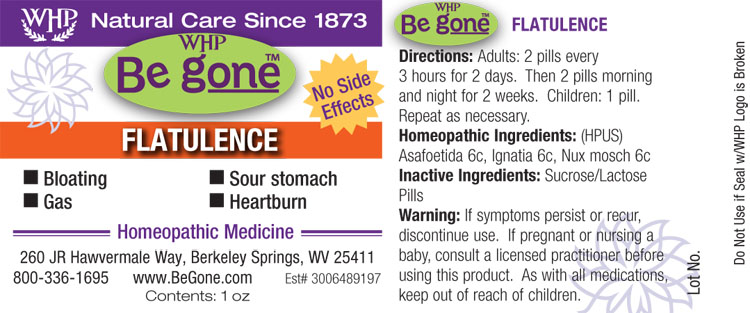 DRUG LABEL: WHP Be gone Flatulence
NDC: 68428-746 | Form: PELLET
Manufacturer: Washington Homeopathic Products
Category: homeopathic | Type: HUMAN OTC DRUG LABEL
Date: 20140508

ACTIVE INGREDIENTS: FERULA ASSA-FOETIDA RESIN 6 [hp_C]/1 1; STRYCHNOS IGNATII SEED 6 [hp_C]/1 1; NUTMEG 6 [hp_C]/1 1
INACTIVE INGREDIENTS: SUCROSE; LACTOSE

DRUG FACTS

ACTIVE INGREDIENTS

ASAFOETIDA

IGNATIA

NUX MOSCH

USES

Relieves the symptoms of flatulence that includes gas, sour stomach, and heartburn. May include abdominal discomfort and bloating accompanied with frequent passing of gas.

KEEP OUT OF REACH OF CHILDREN

As wtih all medications, keep out of reach of children.

INDICATIONS

Asafoetida 6c –offensive odor*

Ignatia 6c –much flatulence*

Nux mosch 6c –indigestion/bloating*

■ Bloating* ■ Gas* ■ Sour stomach* ■ Heartburn*

*These statements have not been reviewed by the Food and Drug Administration.

STOP USE AND ASK DOCTOR

If symptoms persist or recur, discontinue use. If pregnant or nursing a baby, consult a licensed practitioner before using this product.

DIRECTIONS

Adults: 2 pills every 3 hours for 2 days. Then 2 pills morning and night for 2 weeks.

Children: 1 pill. Repeat as necessary.

INACTIVE INGREDIENTS

Sucrose/Lactose Pills